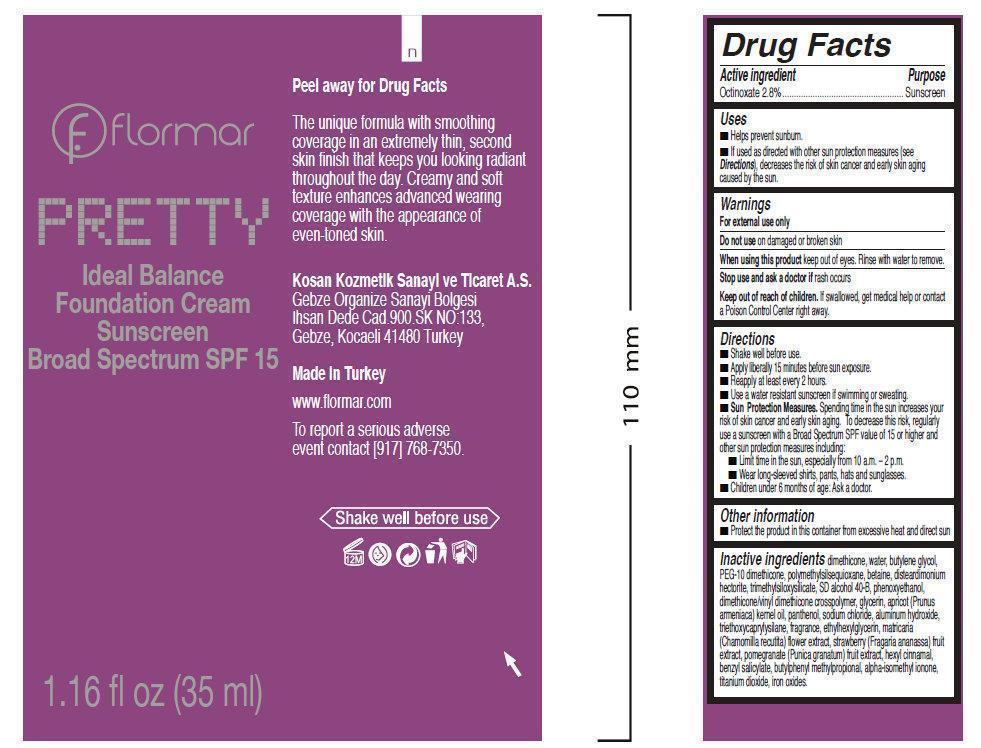 DRUG LABEL: flormar PRETTY Ideal Balance Foundation Sunscreen Broad Spectrum SPF 15 P101 Porcelain
NDC: 61722-100 | Form: CREAM
Manufacturer: Kosan Kozmetik Sanayi ve Ticaret A.S.
Category: otc | Type: HUMAN OTC DRUG LABEL
Date: 20191018

ACTIVE INGREDIENTS: OCTINOXATE 28 mg/1 mL
INACTIVE INGREDIENTS: DIMETHICONE; WATER; BUTYLENE GLYCOL; BETAINE; DISTEARDIMONIUM HECTORITE; PHENOXYETHANOL; GLYCERIN; APRICOT KERNEL OIL; PANTHENOL; SODIUM CHLORIDE; ALUMINUM HYDROXIDE; ETHYLHEXYLGLYCERIN; .ALPHA.-HEXYLCINNAMALDEHYDE; BENZYL SALICYLATE; BUTYLPHENYL METHYLPROPIONAL; ISOMETHYL-.ALPHA.-IONONE; TITANIUM DIOXIDE; FERRIC OXIDE RED

flormar PRETTY Ideal Balance Foundation Cream Sunscreen Broad Spectrum SPF 15 P101 Porcelain

Active Ingredient

Octinoxate 2.8%

Purpose

Sunscreen

Uses

- Helps prevent sunburn.
- If used as directed with other sun protection measures (see Directions), decreases the risk of skin cancer and early skin aging caused by the sun.

Warnings

For external use only

Do not use

on damaged or broken skin

When using this product

keep out of eyes. Rinse with water to remove.

Stop use and ask a doctor if

rash occurs

Keep out of reach of children.

If swallowed, get medical help or contact a Poison Control Center right away.

Directions

- Shake well before use.
- Apply drop by drop with fingertips.
- Apply liberally 15 minutes before sun exposure.
- Reapply at least every 2 hours.
- Use a water resistant sunscreen if swimming or sweating.
- Sun Protection Measures. Spending time in the sun increases your risk of skin cancer and early skin aging. To decrease this risk, regularly use a sunscreen with a Broad Spectrum SPF value of 15 or higher and other sun protection measures including:
-
  - Limit time in the sun, especially from 10 a.m. – 2 p.m.
  - Wear long-sleeved shirts, pants, hats and sunglasses.
- Children under 6 months of age: Ask a doctor.

Other information

- Protect the product in this container from excessive heat and direct sun

Inactive ingredients

Dimethicone, Water, butylene glycol, peg-10 dimethicone, polymethylsilsesquioxane, betaine, disteardimonium hectorite, trimethylsiloxysilicate, sd alcohol 40-b, phenoxyethanol, dimethicone/vinyl dimethicone crosspolymer, glycerin, prunus armeniaca (apricot) kernel oil, panthenol, sodium chloride, aluminum hydroxide, triethoxycaprylysilane, fragrance, ethylhexylglycerin, matricaria (chamomilla recutita) flower extract, strawberry (fragaria ananassa) fruit extract, pomegranate (punica granatum) fruit extract, hexly cinnamal, benzyl salicylate, butylphenyl methylpropional, alpha-isomethyl ionone, titanium dioxide, iron oxides